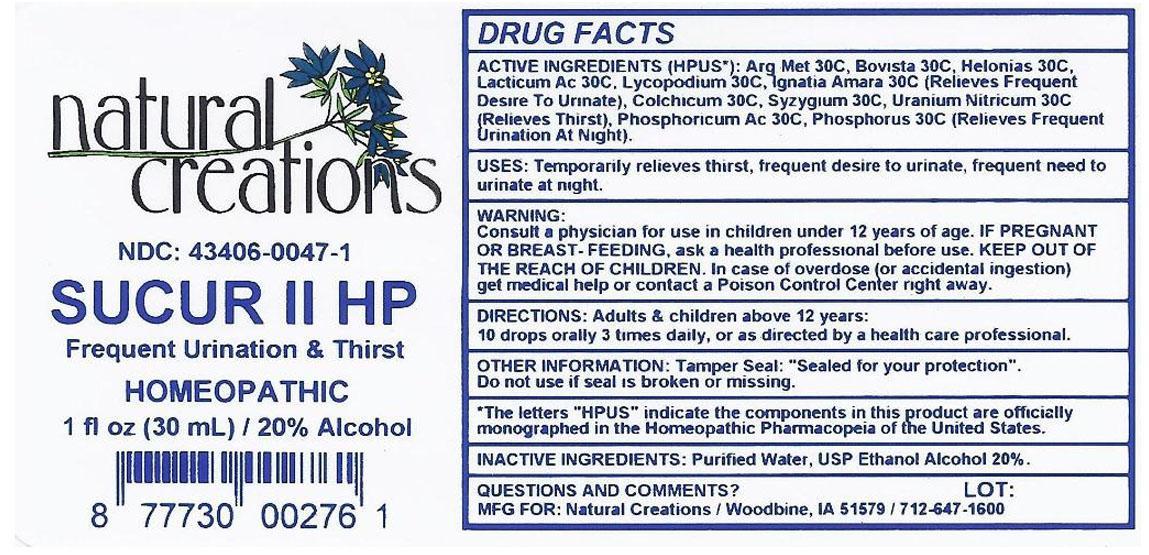 DRUG LABEL: SUCUR II
NDC: 43406-0047 | Form: LIQUID
Manufacturer: Natural Creations, Inc.
Category: homeopathic | Type: HUMAN OTC DRUG LABEL
Date: 20121121

ACTIVE INGREDIENTS: SILVER 30 [hp_C]/1 mL; GIANT PUFFBALL 30 [hp_C]/1 mL; COLCHICUM AUTUMNALE BULB 30 [hp_C]/1 mL; CHAMAELIRIUM LUTEUM ROOT 30 [hp_C]/1 mL; STRYCHNOS IGNATII SEED 30 [hp_C]/1 mL; LACTIC ACID, DL- 30 [hp_C]/1 mL; LYCOPODIUM CLAVATUM SPORE 30 [hp_C]/1 mL; PHOSPHORIC ACID 30 [hp_C]/1 mL; PHOSPHORUS 30 [hp_C]/1 mL; SYZYGIUM CUMINI SEED 30 [hp_C]/1 mL; URANYL NITRATE HEXAHYDRATE 30 [hp_C]/1 mL
INACTIVE INGREDIENTS: WATER; ALCOHOL

SUCUR II HP

ACTIVE INGREDIENT

ACTIVE INGREDIENTS (HPUS*): Argentum Metallicum 30C, Bovista 30C, Colchicum Atumnale 30C, Helonias Dioica 30C, Ignatia Amara 30C, Lacticum Acidum 30C, Lycopodium Clavatum 30C, Phosphoricum Acidum 30C, Phosphorus 30C, Syzygium Jambolanum 30C, Uranium Nitricum 30C

INDICATIONS AND USAGE

USES: Temporarily relieves frequent desire to urinate, frequent need to urinate at night, &/or thirst.

WARNING:

Consult a physician for use in children under 12 years of age. IF PREGNANT OR BREAST-FEEDING, ask a health care professional before use. KEEP OUT OF THE REACH OF CHILDREN. In case of overdose (or accidental ingestion) get medical help or contact a Poison Control Center right away.

DOSAGE AND ADMINISTRATION

DIRECTIONS: Adults and children above 12 years: 10 drops orally 3 times daily, or as directed by a health care professional.

OTHER INFORMATION: Tamper Seal: "Sealed for your protection."

Do not use if seal is broken or missing.

REFERENCES

*The letters "HPUS" indicate the components in the product are officially monographed in the Homeopathic Pharmacopeia of the United States.

INACTIVE INGREDIENTS: Purified Water, USP Ethanol Alcohol 20%

QUESTIONS AND COMMENTS?

MFG FOR: Natural Creations / Woodbine, IA / 51579 712.647.1600

LOT:

PURPOSE

USES: Temporarily relieves frequent desire to urinate, frequent need to urinate at night, &/or thirst.

KEEP OUT OF REACH OF CHILDREN

KEEP OUT OF THE REACH OF CHILDREN. In case of overdose (or accidental ingestion) get medical help or contact a Poison Control Center.

PACKAGE LABEL

NDC: 43406-0047-1

SUCUR II HP

Frequent Urination & Thirst

HOMEOPATHIC

1 fl oz (30 mL) / 20% Alcohol

UPC: 877730002761